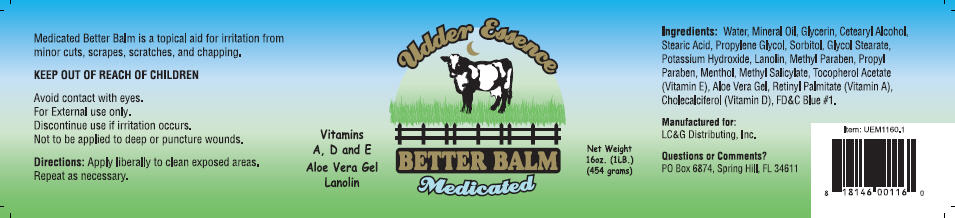 DRUG LABEL: Udder Essence Better Balm Medicated
NDC: 24465-879 | Form: CREAM
Manufacturer: LC&G Distributing Inc.
Category: animal | Type: OTC ANIMAL DRUG LABEL
Date: 20120919

ACTIVE INGREDIENTS: Menthol 0.25 g/100 g; Methyl Salicylate 0.1 g/100 g
INACTIVE INGREDIENTS: Water; Mineral Oil; Glycerin; Cetostearyl Alcohol; Stearic Acid; Propylene Glycol; Sorbitol; Glycol Stearate; Potassium Hydroxide; Lanolin; Methylparaben Sodium; Propylparaben Sodium; .ALPHA.-TOCOPHEROL; Aloe Vera Leaf; Vitamin A; Cholecalciferol; FD&C Blue No. 1

Udder Essence
BETTER BALM
Medicated

PURPOSE

Medicated Better Balm is a topical aid for irritation from minor cuts, scrapes, scratches, and chapping.

WARNINGS

KEEP OUT OF REACH OF CHILDREN

WHEN USING

Avoid contact with eyes.

For External use only.

Discontinue use if irritation occurs.

DO NOT USE

Not to be applied to deep or puncture wounds.

Directions

Apply liberally to clean exposed areas. Repeat as necessary.

Ingredients

Water, Mineral Oil, Glycerin, Cetearyl Alcohol, Stearic Acid, Propylene Glycol, Sorbitol, Glycol Stearate, Potassium Hydroxide, Lanolin, Methyl Paraben, Propyl Paraben, Menthol, Methyl Salicylate, Tocopherol Acetate (Vitamin E), Aloe Vera Gel, Retinyl Palmitate (Vitamin A), Cholecalciferol (Vitamin D), FD&C Blue #1.

Questions or Comments?

PO Box 6874, Spring Hill, FL 34611

PRINCIPAL DISPLAY PANEL - 454 Gram Jar

Vitamins
A, D and E
Aloe Vera Gel
Lanolin

Udder Essence

BETTER BALM
Medicated

Net Weight
16oz. (1LB.)
(454 grams)